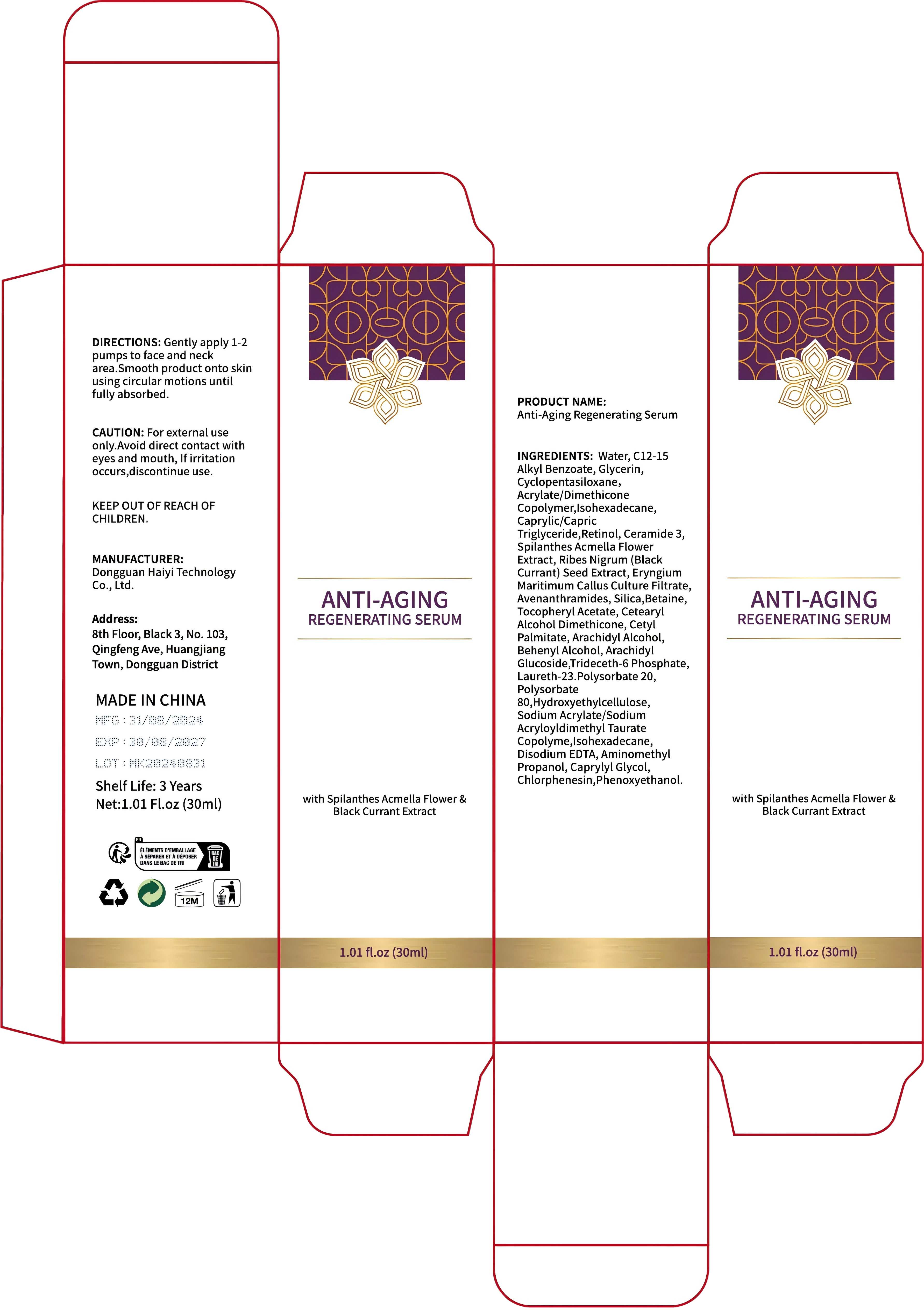 DRUG LABEL: Anti-Aging Regenerating serum
NDC: 84732-075 | Form: LIQUID
Manufacturer: Dongguan Haiyi Technology Co.,Ltd.
Category: otc | Type: HUMAN OTC DRUG LABEL
Date: 20241030

ACTIVE INGREDIENTS: ALKYL (C12-15) BENZOATE 1 mg/30 mL
INACTIVE INGREDIENTS: CAPRYLIC/CAPRIC TRIGLYCERIDE; RIBES NIGRUM SEED; CYCLOPENTASILOXANE; WATER; RETINOL; ACMELLA OLERACEA FLOWER; ISOHEXADECANE; CERAMIDE 3; GLYCERIN

Active ingredient

C12-15Alkyl Benzoate

Inactive ingredient

Water,Glycerin,Cyclopentasiloxane,Acrylate/Dimethicone Copolymer,isohexadecane,Caprylic/CapricTriglyceride,Retinol, Ceramide 3,Spilanthes Acmella FlowerExtract, Ribes Nigrum (BlackCurrant) Seed Extract, EryngiumMaritimum Callus Culture Filtrate,Avenanthramides, Silica,Betaine,Tocopheryl Acetate, CetearylAlcohol Dimethicone, CetylPalmitate,Arachidyl Alcohol,Behenyl Alcohol, ArachidylGlucoside,Trideceth-6 Phosphate,Laureth-23.Polysorbate 20,Polysorbate80,HydroxyethylcelluloseSodium Acrylate/SodiumAcryloyldimethyl TaurateCopolyme,lsohexadecane,Disodium EDTA, Aminomethy!Propanol, Caprylyl Glycol,Chlorphenesin,Phenoxyethanol.

Purpose section

the appearance and health of the skin by targeting signs of aging, such as fine lines, wrinkles, and loss of firmness. This type of serum generally aims to provide hydration, boost skin elasticity, and enhance cell regeneration. Its purpose could be classified as cosmetic, focusing on providing anti-aging benefits and a rejuvenated appearance to the skin.

Warning

1).For external use only, avoid directcontact with eyes, lf you feel any
discomfort, stop using itand wash it with plenty of water. In severe cases,
pleaseseek medical attention in time.
2). Not allowed to be used ondamaged skin,

stop use

This product may cause allergic reactions in asmall number of people.
lf you experience any discomfort,please stop using it immediately.

not use

Not suitable for use by children, pregnantor breast feeding people.

OUT OF CHILDREN

KEEP THE PRODUCT OUT OF REACH OF CHILDREN to

HOW TO USE

Gently apply 1-2pumps to face and neckarea.Smooth product onto skinusing circular motions untilfully absorbed.

Dosage

take an appropriateamount,Use 2-3 times a week